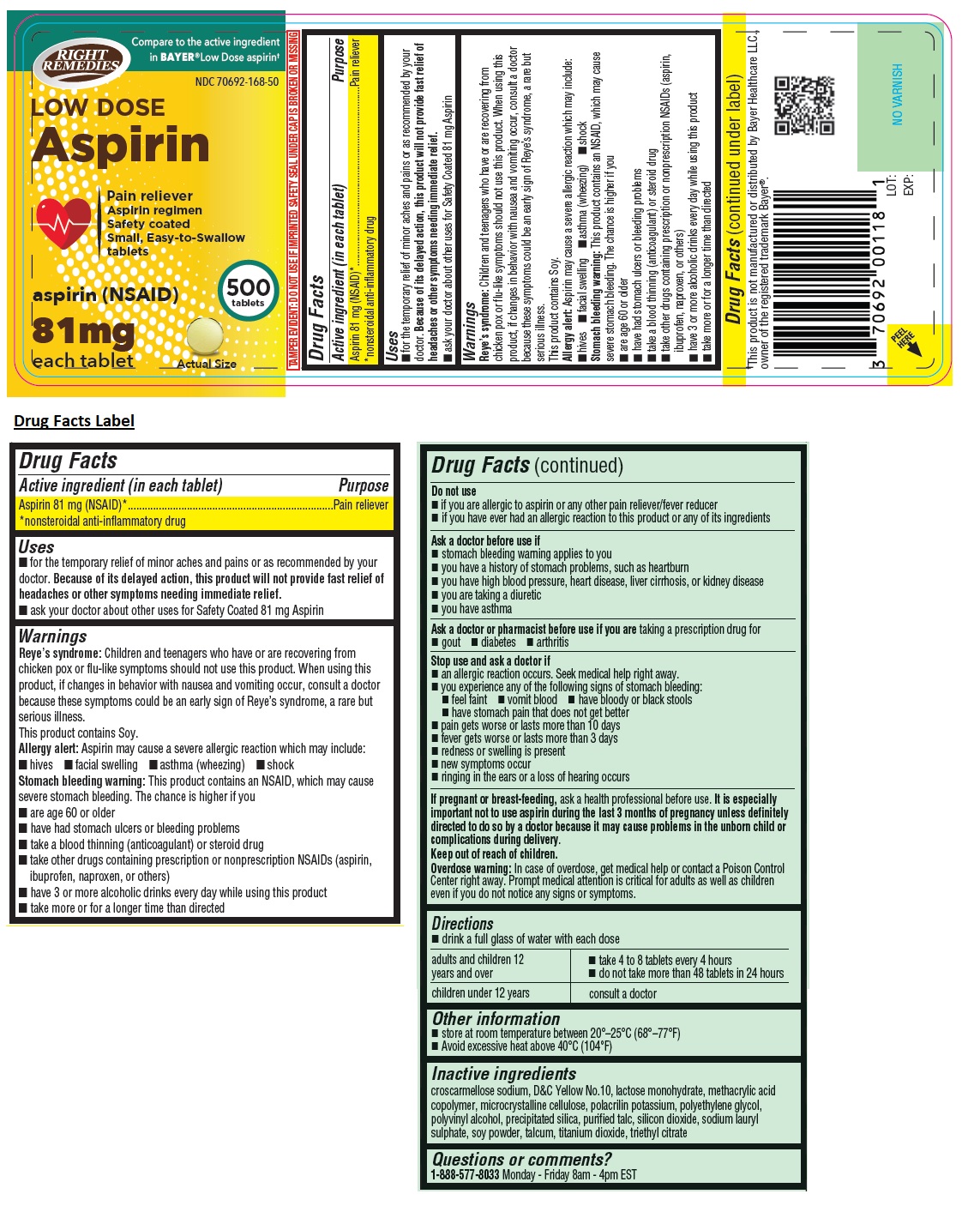 DRUG LABEL: RIGHT REMEDIES LOW DOSE Aspirin 81mg
NDC: 70692-168 | Form: TABLET
Manufacturer: Strive Pharmaceuticals Inc.
Category: otc | Type: HUMAN OTC DRUG LABEL
Date: 20250414

ACTIVE INGREDIENTS: ASPIRIN 81 mg/1 1
INACTIVE INGREDIENTS: CROSCARMELLOSE SODIUM; D&C YELLOW NO. 10; LACTOSE MONOHYDRATE; METHACRYLIC ACID - METHYL METHACRYLATE COPOLYMER (1:1); MICROCRYSTALLINE CELLULOSE; POLACRILIN POTASSIUM; POLYETHYLENE GLYCOL, UNSPECIFIED; POLYVINYL ALCOHOL, UNSPECIFIED; SILICON DIOXIDE; TALC; SODIUM LAURYL SULFATE; SOYBEAN; TITANIUM DIOXIDE; TRIETHYL CITRATE

RIGHT REMEDIES LOW DOSE Aspirin 81mg

Active ingredient (in each tablet)

Aspirin 81 mg (NSAID)*
*nonsteroidal anti-inflammatory drug

Purpose

Pain reliever

Uses

• for the temporary relief of minor aches and pains or as recommended by your doctor. Because of its delayed action, this product will not provide fast relief of headaches or other symptoms needing immediate relief.
• ask your doctor about other uses for Safety Coated 81 mg Aspirin

Warnings

Reye’s syndrome: Children and teenagers who have or are recovering from chicken pox or flu-like symptoms should not use this product. When using this product, if changes in behavior with nausea and vomiting occur, consult a doctor because these symptoms could be an early sign of Reye’s syndrome, a rare but serious illness.

This product contains Soy.
Allergy alert: Aspirin may cause a severe allergic reaction which may include:
• hives • facial swelling • asthma (wheezing) • shock

Stomach bleeding warning: This product contains an NSAID, which may cause severe stomach bleeding. The chance is higher if you
• are age 60 or older
• have had stomach ulcers or bleeding problems
• take a blood thinning (anticoagulant) or steroid drug
• take other drugs containing prescription or nonprescription NSAIDs (aspirin, ibuprofen, naproxen, or others)
• have 3 or more alcoholic drinks every day while using this product
• take more or for a longer time than directed

Do not use
• if you are allergic to aspirin or any other pain reliever/fever reducer
• if you have ever had an allergic reaction to this product or any of its ingredients

Ask a doctor before use if
• stomach bleeding warning applies to you
• you have a history of stomach problems, such as heartburn
• you have high blood pressure, heart disease, liver cirrhosis, or kidney disease
• you are taking a diuretic
• you have asthma

Ask a doctor or pharmacist before use if you are taking a prescription drug for • gout • diabetes • arthritis

Stop use and ask a doctor if
• an allergic reaction occurs. Seek medical help right away.
• you experience any of the following signs of stomach bleeding:
• feel faint • vomit blood • have bloody or black stools
• have stomach pain that does not get better
• pain gets worse or lasts more than 10 days
• fever gets worse or lasts more than 3 days
• redness or swelling is present
• new symptoms occur
• ringing in the ears or a loss of hearing occurs

If pregnant or breast-feeding, ask a health professional before use. It is especially important not to use aspirin during the last 3 months of pregnancy unless definitely directed to do so by a doctor because it may cause problems in the unborn child or complications during delivery.

Keep out of reach of children.

Overdose warning: In case of overdose, get medical help or contact a Poison Control Center right away. Prompt medical attention is critical for adults as well as children even if you do not notice any signs or symptoms.

Directions

• drink a full glass of water with each dose

adults and children 12 years and over | • take 4 to 8 tablets every 4 hours; • do not take more than 48 tablets in 24 hours
children under 12 years | consult a doctor

Other information

• store at room temperature 20°–25°C (68°–77°F)
• Avoid excessive heat above 40°C(104°F)

Inactive ingredients

croscarmellose sodium, D&C Yellow No.10, lactose monohydrate, methacrylic acid copolymer, microcrystalline cellulose, polacrilin potassium, polyethylene glycol, polyvinyl alcohol, precipitated silica, purified talc, silicon dioxide, sodium lauryl sulphate, soy powder, talcum, titanium dioxide, triethyl citrate

Questions or comments?

1-888-577-8033 Monday - Friday 8am - 4pm EST

Compare to the active ingredient in BAYER® Low Dose aspirin†

Pain reliever

Aspirin regimen

Safety coated

Small, Easy-to Swallow tablets

TAMPER EVIDENT: DO NOT USE IF IMPRINTED SAFETY SEAL UNDER CAP IS BROKEN OR MISSING

†This product is not manufactured or distributed by Bayer Healthcare LLC., owner of the registered trademark Bayer®.

Distributed by: Strive Pharmaceuticals Inc.,
East Brunswick, NJ 08816

PRODUCT OF INDIA